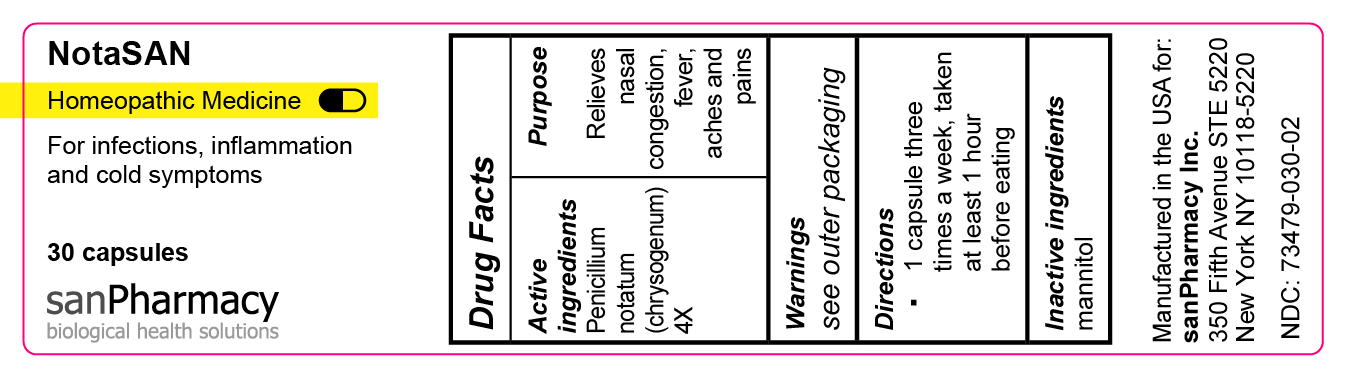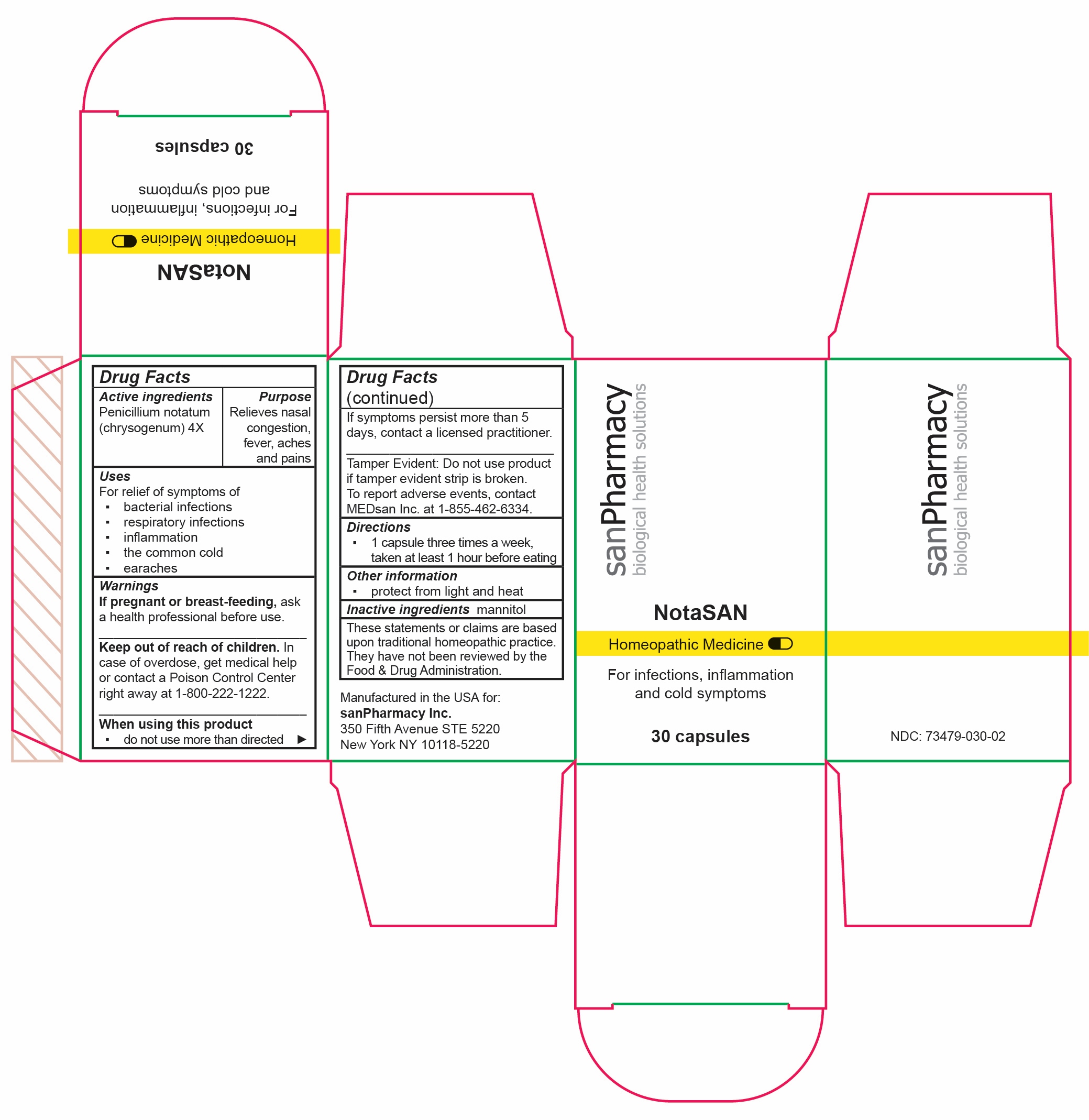 DRUG LABEL: NotaSAN
NDC: 73479-030 | Form: CAPSULE
Manufacturer: sanPharmacy Inc.
Category: homeopathic | Type: HUMAN OTC DRUG LABEL
Date: 20231220

ACTIVE INGREDIENTS: PENICILLIUM CHRYSOGENUM VAR. CHRYSOGENUM 4 [hp_X]/1 1
INACTIVE INGREDIENTS: MANNITOL

NotaSAN Capsules

Indications

For infections, inflammation and cold symptoms

PURPOSE

Relieves nasal congestion, fever, aches and pains

Ingredients

Penicillium notatum (chrysogenum) 4X

INACTIVE INGREDIENT

mannitol

Dosage

1 capsule three times a week, taken at least 1 hour before eating

Warning

If pregnant or breast-feeding, ask a health professional before use.
______________________________
Keep out of reach of children. In case of overdose, get medical help or contact a Poison Control Center right away at 1-800-222-1222.
______________________________
When using this product
▪ do not use more than directed
______________________________
If symptoms persist more than 5 days, contact a licensed practitioner.
______________________________
Tamper Evident: Do not use product if tamper evident strip is broken. To report adverse events, contact MEDsan Inc. at 1-855-462-6334.

Keep out of reach of children. In case of overdose, get medical help or contact a Poison Control Center right away at 1-800-222-1222.

Tamper Evident

Tamper Evident: Do not use product if tamper evident strip is broken. To report adverse events, contact MEDsan Inc. at 1-855-462-6334.

Manufactured in the USA for:
sanPharmacy Inc.
350 Fifth Avenue STE 5220
New York NY 10118-5220

RECENT MAJOR CHANGES

Indications and Usage

Dosage and Administration

Warnings and Precautions

Liability statement

These statements or claims are based upon traditional homeopathic practice. They have not been reviewed by the Food & Drug Administration.

STORAGE AND HANDLING

protect from light and heat

PRINCIPAL DISPLAY PANEL

NotaSAN

Homeopathic Medicine

For infections,

inflammation and

cold symptoms

30 capsules

sanPharmacy

biological health solutions